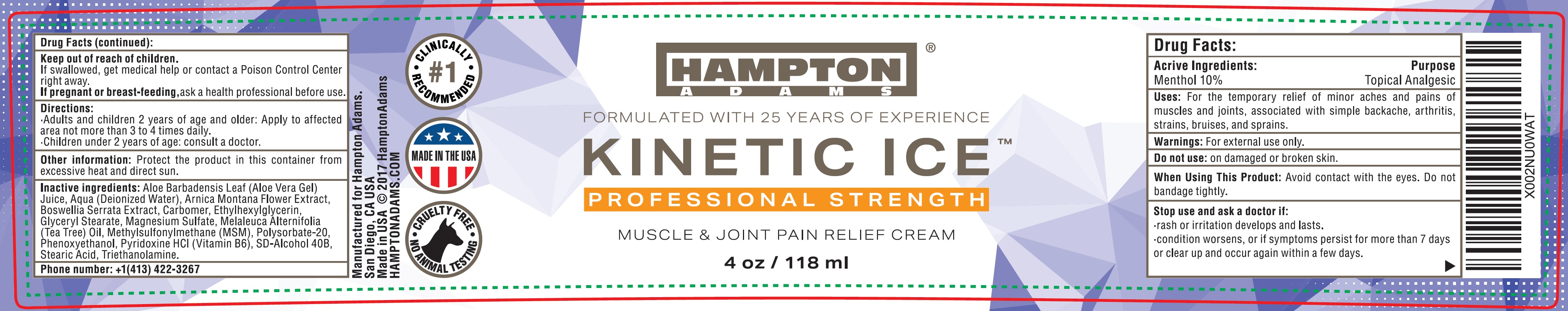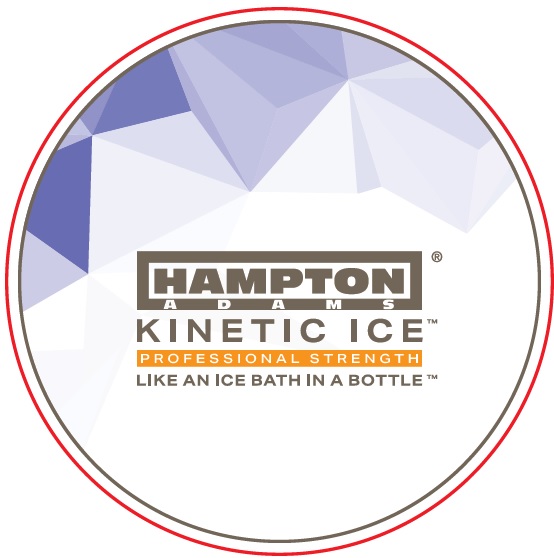 DRUG LABEL: KINETIC ICE Muscle and Joint Pain Relief Cream
NDC: 81050-108 | Form: CREAM
Manufacturer: No Reason, LLC
Category: otc | Type: HUMAN OTC DRUG LABEL
Date: 20231111

ACTIVE INGREDIENTS: MENTHOL 100 mg/1 mL
INACTIVE INGREDIENTS: ALOE VERA LEAF; WATER; ARNICA MONTANA FLOWER; INDIAN FRANKINCENSE; CARBOMER HOMOPOLYMER, UNSPECIFIED TYPE; ETHYLHEXYLGLYCERIN; GLYCERYL MONOSTEARATE; MAGNESIUM SULFATE, UNSPECIFIED FORM; MELALEUCA ALTERNIFOLIA LEAF; DIMETHYL SULFONE; POLYSORBATE 20; PHENOXYETHANOL; PYRIDOXINE HYDROCHLORIDE; ALCOHOL; STEARIC ACID; TROLAMINE

KINETIC ICE Muscle and Joint Pain Relief Cream

Active Ingredients:

Menthol 10%

Purpose

Topical Analgeic

Uses:

For the temporary relief of minor aches and pains of muscles and joints, associated with simple backache, arthritis, strains, bruises, and sprains.

Warnings:

For external use only.

Do not use:

on damaged or broken skin.

When Using This Product:

Avoid contact with the eyes. Do not bandage tightly.

Stop use and ask a doctor if:

- rash or irritation develops and lasts.
- condition worsens, or if symptoms persist for more than 7 days or clear up and occur again within a few days.

Keep out of reach of children.

If swallowed, get medical help or contact a Poison Control Center right away.

If pregnant or breast-feeding,

ask a health professional before use.

Directions:

- Adults and children 2 years of age and older: Apply to affected area not more than 3 to 4 times daily.
- Children under 2 years of age: consult a doctor.

Other information:

Protect the product in this container from excessive heat and direct sun.

Inactive ingredients:

Aloe Barbadensis Leaf (Aloe Vera Gel) Juice, Aqua (Deionized Water), Arnica Montana Flower Extract, Boswellia Serrata Extract, Carbomer, Ethylhexylglycerin, Glyceryl Stearate, Magnesium Sulfate, Melaleuca Alternifolia (Tea Tree) Oil, Methylsulfonylmethane (MSM), Polysorbate-20, Phenoxyethanol, Pyridoxine HCL (Vitamin B6), SD-Alcohol 40B, Stearic Acid, Triethanolamine.

Phone number:

+1(413) 422-3267